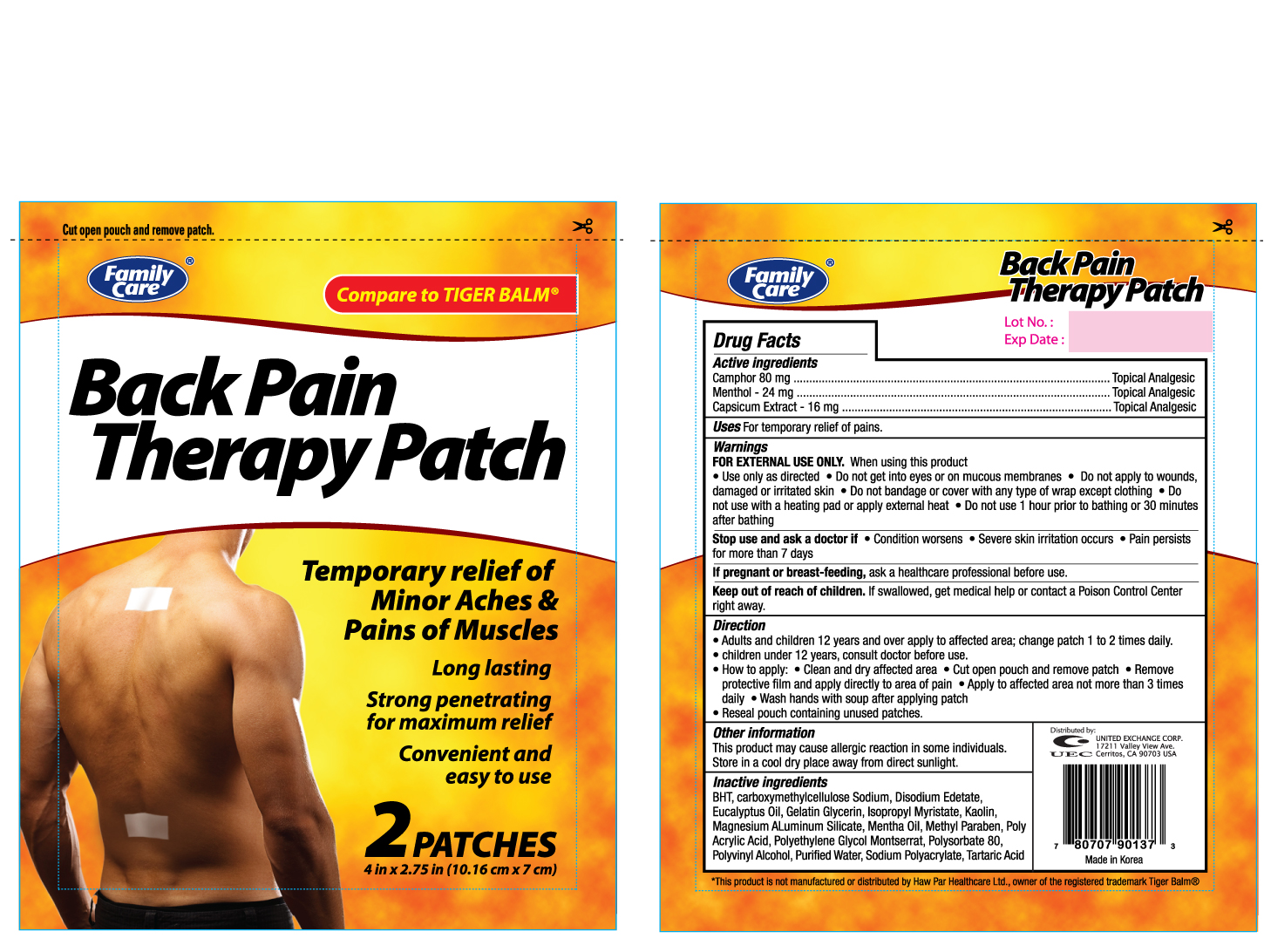 DRUG LABEL: FAMILY CARE BACK PAIN THERAPY
NDC: 65923-901 | Form: PATCH
Manufacturer: UNITED EXCHANGE CORP
Category: otc | Type: HUMAN OTC DRUG LABEL
Date: 20111227

ACTIVE INGREDIENTS: CAMPHOR (SYNTHETIC) 80 mg/1 1; MENTHOL 24 mg/1 1; CAPSICUM OLEORESIN 16 mg/1 1
INACTIVE INGREDIENTS: BUTYLATED HYDROXYTOLUENE; CARBOXYMETHYLCELLULOSE SODIUM; EDETATE DISODIUM; EUCALYPTUS OIL; ISOPROPYL MYRISTATE; KAOLIN; MAGNESIUM ALUMINUM SILICATE; METHYLPARABEN; POLYSORBATE 80; POLYVINYL ALCOHOL; WATER

Drug Facts

Active Ingredients | Purpose
Camphor 80mg / patch | Topical Analgesic
Menthol 24mg / patch | Topical Analgesic
Capsicum Extract 16mg / patch | Topical Analgesic

Uses

For temporary relief of pains.

Warnings

FOR EXTERNAL USE ONLY

When using this product

- Use only as directed
- Do not get into eyes or on mucous membranes
- Do not apply to wounds, damaged or irritated skin
- Do not bandage or cover with any type of wrap except clothing
- Do not use with a heating pad or apply external heat
- Do not use 1 hour prior to bathing or 30 minutes after bathing

Stop use and ask a doctor if

- Condition worsens
- Severe skin irritation occurs
- Pain persists for more than 7 days

PREGNANCY OR BREAST FEEDING

If pregnant or breast-feeding, ask a healthcare professional before use.

Keep out of reach of children. If swallowed, get medical help or contact Poison Control Center right away.

Directions

- Adults and children 12 years and over apply to affected area; change patch 1 to 2 times daily
- Children under 12 years, consult doctor before use
- How to apply:
  - Clean and dry affected area
  - Cut open pouch and remove patch
  - Remove protective film and apply directly to area of pain
  - Apply to affected area not more than 3 times daily
  - Wash hands with soap after applying patch
- Reseal pouch containing unused patches

Other Information

This product may cause allergic reaction in some individuals. Store in cool dry place away from direct sunlight.

Inactive Ingredients

Aluminium glycinate, eucalyptus oil, glycerin, kaolin, mentha oil, polysorbate 80, propylene glycol, sodium carboxymethylcellulose, sodium polyacrylate, polyacrylic acid solution, sorbitol solution, hydrotalcite, water

DOSAGE AND ADMINISTRATION

Distributed By:

UNITED EXCHANGE CORP.

17211 VALLEY VIEW AVE.

CERRITOS, CA 90703

MADE IN KOREA